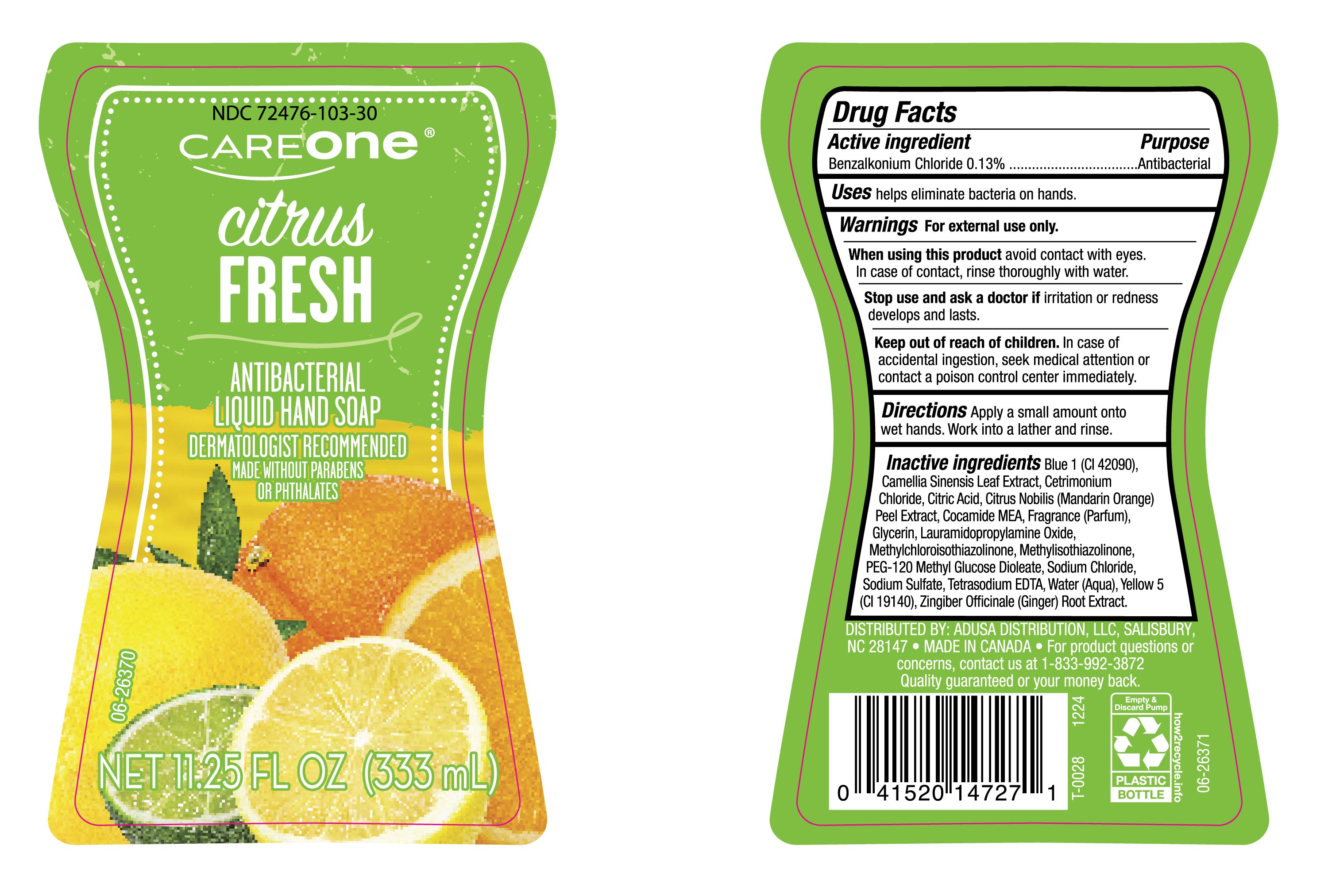 DRUG LABEL: Care One Fresh Citrus
NDC: 72476-103 | Form: LIQUID
Manufacturer: RETAIL BUSINESS SERVICES , LLC
Category: otc | Type: HUMAN OTC DRUG LABEL
Date: 20250119

ACTIVE INGREDIENTS: BENZALKONIUM CHLORIDE 130 mg/100 mL
INACTIVE INGREDIENTS: SODIUM SULFATE; TETRASODIUM EDTA; ZINGIBER OFFICINALE WHOLE; BLUE 1; CAMELLIA SINENSIS LEAF; LAURAMIDOPROPYLAMINE OXIDE; CETRIMONIUM CHLORIDE; COCAMIDE MEA; FRAGRANCE CLEAN ORC0600327; GLYCERIN; METHYLCHLOROISOTHIAZOLINONE; SODIUM CHLORIDE; CITRIC ACID; METHYLISOTHIAZOLINONE; PEG-120 METHYL GLUCOSE DIOLEATE; WATER; YELLOW 5; CITRUS NOBILIS

NDC-72476-103, Careone Citrus Fresh Antibacterial Liquid HandSoap.

Active Ingredient

Benzalkonium Chloride 0.13%

Purpose

Antibacterial

Uses

Helps eliminate bacteria on hands.

Warnings

For external use only

When using this product

Avoid contact with eyes. In case of contact, rinse thoroughly with water.

Stop use and ask a doctor if

irritation or redness develops and lasts.

Keep out of reach of children.

In case of accidental ingestion, seek medical attention or contact a poison control center immediately.

Directions

Apply a small amount onto wet hands. Work into a lather and rinse.

Inactive Ingredients

Blue 1 (CI 42090), Camellia Sinensis Leaf Extract, Cetrimonium Chloride, Citric Acid, Citrus Nobilis (Mandarin Orange) Peel Extract, Cocamide MEA, Fragrance (Parfum), Glycerin, Lauramidopropylamine Oxide, Methylchloroisothiazolinone, Methylisothiazolinone, PEG-120 Methyl Glucose Dioleate, Sodium Chloride, Sodium Sulfate, Tetrasodium EDTA, Water (Aqua), Yellow 5 (CI19140), Zingiber Officinale (Ginger) Root Extract.